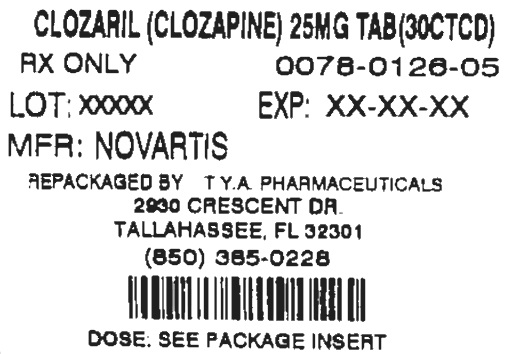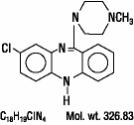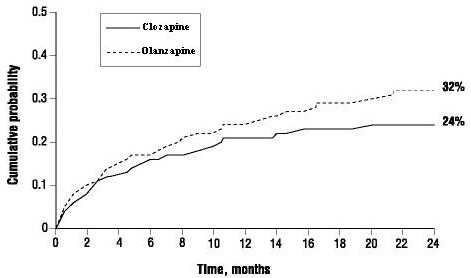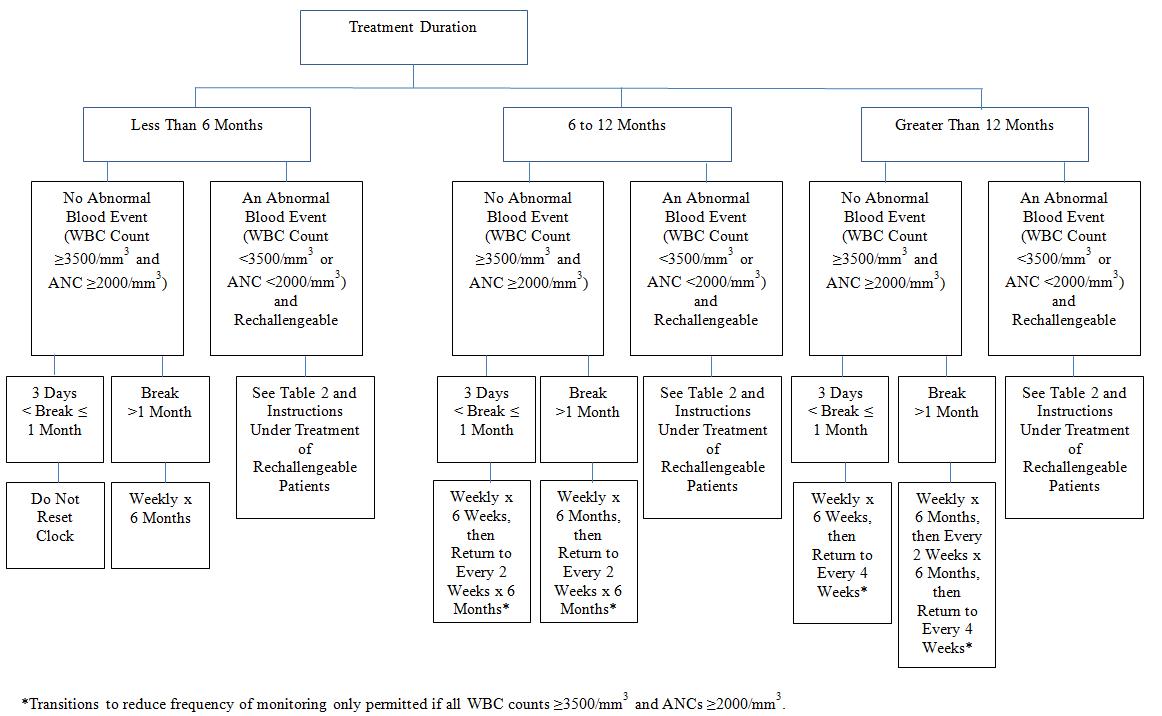 DRUG LABEL: Clozaril
NDC: 64725-1260 | Form: TABLET
Manufacturer: TYA Pharmaceuticals
Category: prescription | Type: HUMAN PRESCRIPTION DRUG LABEL
Date: 20131113

ACTIVE INGREDIENTS: CLOZAPINE 25 mg/1 1
INACTIVE INGREDIENTS: SILICON DIOXIDE; LACTOSE; MAGNESIUM STEARATE; POVIDONES; STARCH, CORN; TALC

HIGHLIGHTS OF PRESCRIBING INFORMATION

These highlights do not include all the information needed to use CLOZARIL safely and effectively. See full prescribing information for CLOZARIL.
CLOZARIL® (clozapine) tablets, for oral use
Initial U.S. Approval: 1989

RECENT MAJOR CHANGES

Dosage and Administration (, ,) 07/2013 2.12.62.7

Contraindications () 07/2013 4

Warnings and Precautions (,) 07/2013 5.25.3

WARNING: AGRANULOCYTOSIS; ORTHOSTATIC HYPOTENSION, BRADYCARDIA, AND SYNCOPE; SEIZURE; MYOCARDITIS AND CARDIOMYOPATHY; INCREASED MORTALITY IN ELDERLY PATIENTS WITH DEMENTIA-RELATED PSYCHOSIS

See full prescribing information for complete boxed warning.

- Agranulocytosis: Can lead to serious infection and death. Monitor white blood cell count and absolute neutrophil count prior to and during treatment. Monitor for symptoms of agranulocytosis and infection. (,) 2.15.1
- Because of risk of agranulocytosis, CLOZARIL is available only through a restricted program called the CLOZARIL National Registry. Prescribers, patients, and pharmacies must enroll in the program. () 5.2
- Orthostatic Hypotension, Bradycardia, and Syncope: Risk is dose-related. Starting dose is 12.5 mg. Titrate gradually and use divided dosages. (, ,) 2.22.55.3
- Seizure: Risk is dose-related. Titrate gradually and use divided doses. Use with caution in patients with history of seizure or risk factors for seizure. (,) 2.25.4
- Myocarditis and Cardiomyopathy: Can be fatal. Discontinue and obtain cardiac evaluation if findings suggest these cardiac reactions. () 5.5
- Increased Mortality in Elderly Patients with Dementia-Related Psychosis: CLOZARIL is not approved for this condition. () 5.6

1 INDICATIONS AND USAGE

CLOZARIL is an atypical antipsychotic indicated for:

- Treatment-resistant schizophrenia. Efficacy was established in an active-controlled study. (,) 1.114.1
- Reducing suicidal behavior in patients with schizophrenia or schizoaffective disorder. Efficacy was established in an active-controlled study. (,) 1.214.2

2 DOSAGE AND ADMINISTRATION

- Starting Dose: 12.5 mg once daily or twice daily. () 2.2
- Use cautious titration and divided dosage schedule. (,) 2.25.3
- Titration: increase the total daily dosage in increments of 25 mg to 50 mg per day, if well-tolerated. () 2.2
- Target dose: 300 mg to 450 mg per day, in divided doses, by the end of 2 weeks. () 2.2
- Subsequent increases: increase in increments of 100 mg or less, once or twice weekly. () 2.2
- Maximum daily dose: 900 mg () 2.2

3 DOSAGE FORMS AND STRENGTHS

25 mg and 100 mg tablets with a facilitated score on one side () 3

4 CONTRAINDICATIONS

- History of clozapine-induced agranulocytosis or severe Granulocytopenia. () 4
- Known hypersensitivity to clozapine or any other component of CLOZARIL. () 4

5 WARNINGS AND PRECAUTIONS

- Assess for organ involvement (e.g., myocarditis, pancreatitis, hepatitis, colitis, nephritis). Discontinue if these occur. () Eosinophilia:5.7
- Can be fatal. Consider additional risk factors for prolonged QT interval (disorders and drugs). () QT Interval Prolongation:5.8
- Atypical antipsychotic drugs have been associated with metabolic changes that may increase cardiovascular/ cerebrovascular risk. These metabolic changes include: Metabolic Changes:
  - Monitor for symptoms of hyperglycemia including polydipsia, polyuria, polyphagia, and weakness. Monitor glucose regularly in patients with diabetes or at risk for diabetes. () Hyperglycemia and Diabetes Mellitus:5.9
  - Undesirable alterations in lipids have occurred in patients treated with atypical antipsychotics. () Dyslipidemia:5.9
  - Significant weight gain has occurred. Monitor weight gain. () Weight Gain:5.9
- Immediately discontinue and monitor closely. Assess for co-morbid conditions. () Neuroleptic Malignant Syndrome (NMS):5.10
- Evaluate for infection, agranulocytosis, NMS. () Fever:5.11
- Consider PE if respiratory distress, chest pain, or deep vein thrombosis occur. () Pulmonary Embolism (PE):5.12
- Use cautiously in presence of specific conditions (e.g., narrow angle glaucoma, use of anticholinergic drugs). () Anticholinergic Toxicity:5.13
- Advise caution when operating machinery, including automobiles. () Interference with Cognitive and Motor Performance:5.14

6 ADVERSE REACTIONS

Most common adverse reactions (≥5%) were: CNS reactions (sedation, dizziness/vertigo, headache, and tremor); cardiovascular reactions (tachycardia, hypotension, and syncope); autonomic nervous system reactions (hypersalivation, sweating, dry mouth, and visual disturbances); gastrointestinal reactions (constipation and nausea); and fever. () 6.1
To report SUSPECTED ADVERSE REACTIONS, contact Novartis Pharmaceuticals Corporation at 1-888-669-6682 or FDA at 1-800-FDA-1088 or www.fda.gov/medwatch.

7 DRUG INTERACTIONS

- Reduce CLOZARIL dose to one-third when coadministered with strong CYP1A2 inhibitors (e.g., fluvoxamine, ciprofloxacin, enoxacin). (,) Concomitant use of Strong CYP1A2 Inhibitors:2.67.1
- Concomitant use of is not recommended. (,) Strong CYP3A4 Inducers 2.67.1
- Consider reducing CLOZARIL dose when CYP1A2 (e.g., tobacco smoke) or CYP3A4 inducers (e.g., carbamazepine) are discontinued. (,) Discontinuation of CYP1A2 or CYP3A4 Inducers:2.67.1

8 USE IN SPECIFIC POPULATIONS

- Discontinue drug or discontinue nursing, taking into consideration importance of drug to mother. () Nursing Mothers:8.3

FULL PRESCRIBING INFORMATION

WARNING: AGRANULOCYTOSIS; ORTHOSTATIC HYPOTENSION, BRADYCARDIA, AND SYNCOPE; SEIZURE; MYOCARDITIS AND CARDIOMYOPATHY; INCREASED MORTALITY IN ELDERLY PATIENTS WITH DEMENTIA-RELATED PSYCHOSIS

Agranulocytosis

CLOZARIL treatment has caused agranulocytosis, defined as an absolute neutrophil count (ANC) less than 500/mm . Agranulocytosis can lead to serious infection and death. Prior to initiating treatment with CLOZARIL, obtain a baseline white blood cell (WBC) count and ANC. The ANC must be greater than or equal to 2000/mm and the WBC must be greater than or equal to 3500/mm for a patient to begin treatment with CLOZARIL. During treatment, patients must have regular monitoring of ANC and WBC. Discontinue CLOZARIL and do not rechallenge if the ANC is less than 1000/mm or the WBC is less than 2000/mm . Advise patients to immediately report symptoms consistent with agranulocytosis or infection (e.g., fever, weakness, lethargy, or sore throat) .^3^3^3^3^3 [see Dosage and Administration (2.1) and Warnings and Precautions (5.1)]

Because of the risk of agranulocytosis, CLOZARIL is available only through a restricted program called the CLOZARIL National Registry. Under the CLOZARIL National Registry, prescribers, patients, and pharmacies must enroll in the program . [see Warnings and Precautions (5.2)]

Orthostatic Hypotension, Bradycardia, Syncope

Orthostatic hypotension, bradycardia, syncope, and cardiac arrest have occurred with CLOZARIL treatment. The risk is highest during the initial titration period, particularly with rapid dose escalation. These reactions can occur with the first dose, with doses as low as 12.5 mg per day. Initiate treatment at 12.5 mg once or twice daily; titrate slowly; and use divided dosages. Use CLOZARIL cautiously in patients with cardiovascular or cerebrovascular disease or conditions predisposing to hypotension (e.g., dehydration, use of antihypertensive medications) . [see Dosage and Administration (2.2, and 2.5) and Warnings and Precautions (5.3)]

Seizures

Seizures have occurred with CLOZARIL treatment. The risk is dose-related. Initiate treatment at 12.5 mg, titrate gradually, and use divided dosing. Use caution when administering CLOZARIL to patients with a history of seizures or other predisposing risk factors for seizure (CNS pathology, medications that lower the seizure threshold, alcohol abuse). Caution patients about engaging in any activity where sudden loss of consciousness could cause serious risk to themselves or others . [see Dosage and Administration (2.2), Warnings and Precautions (5.4)]

Myocarditis and Cardiomyopathy

Fatal myocarditis and cardiomyopathy have occurred with CLOZARIL treatment. Discontinue CLOZARIL and obtain a cardiac evaluation upon suspicion of these reactions. Generally, patients with CLOZARIL-related myocarditis or cardiomyopathy should not be rechallenged with CLOZARIL. Consider the possibility of myocarditis or cardiomyopathy if chest pain, tachycardia, palpitations, dyspnea, fever, flu-like symptoms, hypotension, or ECG changes occur . [see Warnings and Precautions (5.5)]

Increased Mortality in Elderly Patients with Dementia-Related Psychosis

Elderly patients with dementia-related psychosis treated with antipsychotic drugs are at an increased risk of death. CLOZARIL is not approved for use in patients with dementia-related psychosis . [see Warnings and Precautions (5.6)]

1 INDICATIONS AND USAGE

1.1 Treatment Resistant Schizophrenia

CLOZARIL is indicated for the treatment of severely ill patients with schizophrenia who fail to respond adequately to standard antipsychotic treatment. Because of the significant risk of agranulocytosis and seizure associated with its use, CLOZARIL should be used only in patients who have failed to respond adequately to standard antipsychotic treatment . [see Warnings and Precautions (5.1, 5.4)]

The effectiveness of CLOZARIL in treatment-resistant schizophrenia was demonstrated in a 6-week, randomized, double-blind, active-controlled study comparing CLOZARIL and chlorpromazine in patients who had failed other antipsychotics . [see Clinical Studies (14.1)]

1.2 Reduction in the Risk of Recurrent Suicidal Behavior in Schizophrenia or Schizoaffective Disorder

CLOZARIL is indicated for reducing the risk of recurrent suicidal behavior in patients with schizophrenia or schizoaffective disorder who are judged to be at chronic risk for re-experiencing suicidal behavior, based on history and recent clinical state. Suicidal behavior refers to actions by a patient that put him/herself at risk for death.

The effectiveness of CLOZARIL in reducing the risk of recurrent suicidal behavior was demonstrated over a 2-year treatment period in the InterSePT trial .TM [see Clinical Studies (14.2)]

2 DOSAGE AND ADMINISTRATION

2.1 Required Laboratory Testing Prior to Initiation and During Therapy

Prior to initiating treatment with CLOZARIL, obtain a complete blood count (CBC) with differential. The absolute neutrophil count (ANC) must be greater than or equal to 2000/mm and the WBC must be greater than or equal to 3500 mm in order to initiate treatment. To continue treatment, the ANC and WBC must be monitored regularly .^3^3 [see Warnings and Precautions (5.1)]

2.2 Dosing Information

The starting dose is 12.5 mg once daily or twice daily. The total daily dose can be increased in increments of 25 mg to 50 mg per day, if well-tolerated, to achieve a target dose of 300 mg to 450 mg per day (administered in divided doses) by the end of 2 weeks. Subsequently, the dose can be increased once weekly or twice weekly, in increments of up to 100 mg. The maximum dose is 900 mg per day. To minimize the risk of orthostatic hypotension, bradycardia, and syncope, it is necessary to use this low starting dose, gradual titration schedule, and divided dosages . [see Warnings and Precautions (5.3)]

CLOZARIL can be taken with or without food . [see Pharmacokinetics (12.3)]

2.3 Maintenance Treatment

Generally, it is recommended that patients responding to CLOZARIL continue maintenance treatment on their effective dose beyond the acute episode.

2.4 Discontinuation of Treatment

In the event of planned termination of CLOZARIL therapy, reduce the dose gradually over a period of 1 to 2 weeks. If abrupt discontinuation is necessary (because of agranulocytosis or another medical condition, for example), monitor carefully for the recurrence of psychotic symptoms and symptoms related to cholinergic rebound such as profuse sweating, headache, nausea, vomiting, and diarrhea.

2.5 Re-Initiation of Treatment

When restarting CLOZARIL in patients who have discontinued CLOZARIL (i.e., 2 days or more since the last dose), re-initiate with 12.5-mg once daily or twice daily. This is necessary to minimize the risk of hypotension, bradycardia, and syncope . If that dose is well tolerated, the dose may be increased to the previously therapeutic dose more quickly than recommended for initial treatment. [see Warnings and Precautions (5.3)]

2.6 Dosage Adjustments with Concomitant use of CYP1A2, CYP2D6, CYP3A4 Inhibitors or CYP1A2, CYP3A4 Inducers

Dose adjustments may be necessary in patients with concomitant use of: strong CYP1A2 inhibitors (e.g., fluvoxamine, ciprofloxacin, or enoxacin); moderate or weak CYP1A2 inhibitors (e.g., oral contraceptives, or caffeine); CYP2D6 or CYP3A4 inhibitors (e.g., cimetidine, escitalopram, erythromycin, paroxetine, bupropion, fluoxetine, quinidine, duloxetine, terbinafine, or sertraline); CYP3A4 inducers (e.g., phenytoin, carbamazepine, St. John’s wort, and rifampin); or CYP1A2 inducers (e.g., tobacco smoking) (Table 1) . [see Drug Interactions (7)]

Table 1. Dose Adjustment in Patients Taking Concomitant Medications
Comedications | Scenarios
 | Initiating CLOZARIL while taking a comedication | Adding a comedication while taking CLOZARIL | Discontinuing a comedication while continuing CLOZARIL
Strong CYP1A2 Inhibitors | Use one-third of the CLOZARIL dose. |  | Increase CLOZARIL dose based on clinical response.
Moderate or Weak CYP1A2 Inhibitors | Monitor for adverse reactions. Consider reducing the CLOZARIL dose if necessary. |  | Monitor for lack of effectiveness. Consider increasing CLOZARIL dose if necessary.
CYP2D6 or CYP3A4 Inhibitors |  |  | Monitor for lack of effectiveness. Consider increasing CLOZARIL dose if necessary.
Strong CYP3A4 Inducers | Concomitant use is not recommended. However, if the inducer is necessary, it may be necessary to increase the CLOZARIL dose. Monitor for decreased effectiveness. |  | Reduce CLOZARIL dose based on clinical response.
Moderate or weak CYP1A2 or CYP3A4 Inducers | Monitor for decreased effectiveness. Consider increasing the CLOZARIL dose if necessary. |  | Monitor for adverse reactions. Consider reducing the CLOZARIL dose if necessary.

2.7 Renal or Hepatic Impairment or CYP2D6 Poor Metabolizers

It may be necessary to reduce the CLOZARIL dose in patients with significant renal or hepatic impairment, or in CYP2D6 poor metabolizers . [see Use in Specific Populations (8.6, 8.7)]

3 DOSAGE FORMS AND STRENGTHS

CLOZARIL (clozapine) is available as 25 mg and 100 mg round, pale-yellow, uncoated tablets with a facilitated score on one side.

4 CONTRAINDICATIONS

- History of Clozapine-induced Agranulocytosis or Severe Granulocytopenia

CLOZARIL is contraindicated in patients with a history of clozapine-induced agranulocytosis or severe granulocytopenia . [see Warnings and Precautions (5.1)]

- Hypersensitivity

CLOZARIL is contraindicated in patients with a history of hypersensitivity to clozapine (e.g., photosensitivity, vasculitis, erythema multiforme, or Stevens-Johnson syndrome) or any other component of CLOZARIL . [see Adverse Reactions (6.2)]

5 WARNINGS AND PRECAUTIONS

5.1 Agranulocytosis

Background

Agranulocytosis, defined as an ANC of less than 500/mm , has been estimated to occur in association with clozapine use at a cumulative incidence at 1 year of approximately 1.3%, based on the occurrence of 15 US cases out of 1743 patients exposed to CLOZARIL during its clinical testing prior to domestic marketing. All of these cases occurred at a time when the need for close monitoring of WBC counts was already recognized. A hematologic risk analysis was conducted based upon the available information in the CLOZARIL National Registry for US patients. Based upon a cut-off date of April 30, 1995, the incidence rates of agranulocytosis based upon a weekly monitoring schedule rose steeply during the first 2 months of therapy, peaking in the third month. Among clozapine patients who continued the drug beyond the third month, the weekly incidence of agranulocytosis fell a substantial degree. After 6 months, the weekly incidence of agranulocytosis declines still further; however, it never reaches zero. It should be noted that any type of reduction in the frequency of monitoring WBC counts may result in an increased incidence of agranulocytosis.^3

Risk Factors

Experience from clinical development, as well as from examples in the medical literature, suggests that patients who have developed agranulocytosis during clozapine therapy are at increased risk of subsequent episodes of agranulocytosis. Analysis of WBC count data from the CLOZARIL National Registry also suggests that patients who have an initial episode of moderate leukopenia (3000/mm >WBC count ≥2000/mm) are at an increased risk of subsequent episodes of agranulocytosis. Except for bone-marrow suppression during initial clozapine therapy, there are no other established risk factors based on worldwide experience for the development of agranulocytosis in association with clozapine use. However, a disproportionate number of the US cases of agranulocytosis occurred in patients of Jewish background compared to the overall proportion of such patients exposed during domestic development of clozapine. Most of the US cases of agranulocytosis occurred within 4–10 weeks of exposure, but neither dose nor duration is a reliable predictor of this problem. Agranulocytosis associated with other antipsychotic drugs has been reported to occur with a greater frequency in women, the elderly, and in patients who are cachectic or have serious underlying medical illness; such patients may also be at particular risk with clozapine, although this has not been definitively demonstrated.^3^3

WBC Count and ANC Clinical Monitoring Schedule

CLOZARIL is available only through a distribution system that ensures monitoring of WBC count and ANC according to the schedule described below prior to delivery of the next supply of medication.

As described in Table 2, patients who are being treated with CLOZARIL must have a baseline WBC count and ANC before initiation of treatment, and a WBC count and ANC every week for the first 6 months. Thereafter, if acceptable WBC counts and ANCs (WBC count ≥3500/mm and ANC ≥2000/mm) have been maintained during the first 6 months of continuous therapy, WBC counts and ANCs can be monitored every 2 weeks for the next 6 months. Thereafter, if acceptable WBC counts and ANCs (WBC count ≥3500/mm and ANC ≥2000/mm) have been maintained during the second 6 months of continuous therapy, WBC count and ANC can be monitored every 4 weeks.^3^3^3^3

When treatment with CLOZARIL is discontinued (regardless of the reason), WBC count and ANC must be monitored weekly for at least 4 weeks from the day of discontinuation or until WBC count ≥3500/mm and ANC ≥2000/mm .^3^3

Table 2 provides a summary of the frequency of monitoring that should occur based on various stages of therapy (e.g., initiation of therapy) or results from WBC count and ANC monitoring tests (e.g., moderate leukopenia). The text that follows should be consulted for additional details regarding the treatment of patients under the various conditions (e.g., severe leukopenia).

Advise patients to immediately report the appearance of signs/symptoms consistent with agranulocytosis or infection (e.g., fever, weakness, lethargy, or sore throat) at any time during CLOZARIL therapy. Such patients should have a WBC count and an ANC performed promptly.

Table 2. Frequency of Monitoring Based on Stage of Therapy or Results from WBC Count and ANC Monitoring Tests
Situation | Hematological Values for Monitoring | Frequency of WBC Count and ANC Monitoring
Initiation of therapy | WBC count≥3500/mm and ANC≥2000/mm Note: Do not initiate in patients with a history of clozapine-induced agranulocytosis or severe granulocytopenia.^3 ^3 | Weekly for 6 months
6 to 12 months of therapy | WBC ≥3500/mm and ANC ≥2000/mm^3 ^3 | Every 2 weeks for 6 months
12 months of therapy | WBC ≥3500/mm and ANC ≥2000/mm^3 ^3 | Every 4 weeks ad infinitum
Immature forms present | N/A | Repeat WBC and ANC
Discontinuation of therapy | N/A | Weekly for at least 4 weeks from day of discontinuation or until WBC ≥3500/mm and ANC ≥2000/mm^3^3
Substantial drop in WBC or ANC | Single drop or cumulative drop within 3 weeks of: WBC ≥3000/mm or ANC ≥1500/mm ^3 ^3 | 1. Repeat WBC and ANC 2. If repeat values are: WBC 3000/mm to 3500 and ANC >2000/mm , then monitor twice weekly^3^3
Mild leukopenia and/or Mild granulocytopenia | If WBC 3000 mm to <3500/mm and/or ANC 1500/mm to <2000/mm^3 ^3 ^3 ^3 | Twice weekly until WBC >3500/mm and ANC >2000/mm then return to previous monitoring frequency^3^3
Moderate leukopenia and/or Moderate granulocytopenia | WBC 2000/mm to <3000/mm and/or ANC 1000/mm to <1500/mm^3 ^3 ^3 ^3 | 1. Interrupt therapy 2. Daily until WBC >3000/mm and ANC >1500/mm^3^3 3. Twice weekly until WBC >3500/mm and ANC >2000/mm^3^3 4. May rechallenge when WBC >3500/mm and ANC >2000/mm^3^3 5. If rechallenged, monitor weekly for 1 year before returning to the usual monitoring schedule of every 2 weeks for 6 months and then every 4 weeks ad infinitum
Severe leukopenia and/or Severe granulocytopenia | WBC count <2000/mm and/or ANC <1000/mm^3 ^3 | 1. Discontinue treatment and do not rechallenge patient 2. Monitor until normal and for at least 4 weeks from day of discontinuation as follows: - Daily until WBC >3000/mm and ANC >1500/mm^3^3 - Twice weekly until WBC >3500/mm and ANC >2000/mm^3^3 - Weekly after WBC >3500/mm^3
Agranulocytosis | ANC <500/mm^3 | 1. Discontinue treatment and do not rechallenge patient 2. Monitor until normal and for at least 4 weeks from day of discontinuation as follows: - Daily until WBC >3000/mm and ANC >1500/mm^3^3 - Twice weekly until WBC >3500/mm and ANC >2000/mm^3^3 - Weekly after WBC >3500/mm^3
WBC=White blood cell
ANC=Absolute neutrophil count

Decrements in WBC Count and/or ANC

Consult Table 2 above to determine how to monitor patients who experience decrements in WBC count and/or ANC at any point during treatment. Additionally, patients should be carefully monitored for flu-like symptoms or other symptoms suggestive of infection.

Nonrechallengeable Patients

If the total WBC count falls below 2000/mm or the ANC falls below 1000/mm , bone-marrow aspiration should be considered to ascertain granulopoietic status and patients should not be rechallenged with clozapine. Protective isolation with close observation may be indicated if granulopoiesis is determined to be deficient. Should evidence of infection develop, the patient should have appropriate cultures performed and an appropriate antibiotic regimen instituted.^3^3

Patients discontinued from clozapine therapy due to significant granulopoietic suppression have been found to develop agranulocytosis upon rechallenge, often with a shorter latency on re-exposure. To reduce the chances of rechallenge occurring in patients who have experienced significant bone-marrow suppression during clozapine therapy, a single, national master file (i.e., Nonrechallengeable Database) is confidentially maintained.

Treatment of Rechallengeable Patients

Patients may be rechallenged with clozapine if their WBC count does not fall below 2000/mm and the ANC does not fall below 1000/mm . However, analysis of the data from the CLOZARIL National Registry suggests that patients who have an initial episode of moderate leukopenia (3000/mm >WBC count ≥2000/mm) have up to a 12-fold increased risk of having a subsequent episode of agranulocytosis when rechallenged as compared to the full cohort of patients treated with clozapine. Although CLOZARIL therapy may be resumed if no symptoms of infection develop and when the WBC count rises above 3500/mm and the ANC rises above 2000/mm , prescribers are strongly advised to consider whether the benefit of continuing CLOZARIL treatment outweighs the increased risk of agranulocytosis.^3^3^3^3^3^3

Analyses of the CLOZARIL National Registry have shown an increased risk of having a subsequent episode of granulopoietic suppression up to a year after recovery from the initial episode. Therefore, as noted in Table 2, patients must undergo weekly WBC count and ANC monitoring for 1 year following recovery from an episode of moderate leukopenia and/or moderate granulocytopenia regardless of when the episode develops. If acceptable WBC counts and ANC (WBC count ≥3500/mm and ANC ≥2000/mm) have been maintained during the year of weekly monitoring, WBC counts can be monitored every 2 weeks for the next 6 months. If acceptable WBC counts and ANC (WBC count ≥3500/mm and ANC ≥2000/mm) continue to be maintained during the 6 months of every 2-week monitoring, WBC counts can be monitored every 4 weeks thereafter, ad infinitum.^3^3^3^3

Interruptions in Therapy

Figure 1 provides instructions regarding re-initiating therapy and subsequently the frequency of WBC count and ANC monitoring after a period of interruption.

Figure 1. Resuming Monitoring Frequency after Interruption of Therapy

5.2 CLOZARIL National Registry Because of the Risk of Agranulocytosis

Because of the risk of agranulocytosis, CLOZARIL is available only through a restricted program called the CLOZARIL National Registry. Under the CLOZARIL National Registry, prescribers, patients, pharmacies, and distributors must enroll in the program.

Required components of the CLOZARIL National Registry are:

- Healthcare professionals who prescribe CLOZARIL must enroll in the program and comply with the Registry requirements.
- Pharmacies that dispense CLOZARIL must enroll in the program and comply with the Registry requirements.
- Routine monitoring and submission of laboratory results (WBC and ANC) is required during treatment with CLOZARIL . [see Warnings and Precautions (5.1)]
- Patients who receive CLOZARIL must be enrolled in a registry.

Further information is available at or 1-888-669-6682. http://www.clozarilregistry.com

5.3 Orthostatic Hypotension, Bradycardia, and Syncope

Hypotension, bradycardia, syncope, and cardiac arrest have occurred with clozapine treatment. The risk is highest during the initial titration period, particularly with rapid dose-escalation. These reactions can occur with the first dose, at doses as low as 12.5 mg. These reactions can be fatal. The syndrome is consistent with neurally mediated reflex bradycardia (NMRB).

Treatment must begin at a maximum dose of 12.5 mg once daily or twice daily. The total daily dose can be increased in increments of 25 mg to 50 mg per day, if well-tolerated, to a target dose of 300 mg to 450 mg per day (administered in divided doses) by the end of 2 weeks. Subsequently, the dose can be increased weekly or twice weekly, in increments of up to 100 mg. The maximum dose is 900 mg per day. Use cautious titration and a divided dosage schedule to minimize the risk of serious cardiovascular reactions . Consider reducing the dose if hypotension occurs. When restarting patients who have had even a brief interval off CLOZARIL (i.e., 2 days or more since the last dose), re-initiate treatment at 12.5 mg once daily or twice daily . [see Dosage and Administration (2.2)] [see Dosage and Administration (2.5)]

Use CLOZARIL cautiously in patients with cardiovascular disease (history of myocardial infarction or ischemia, heart failure, or conduction abnormalities), cerebrovascular disease, and conditions which would predispose patients to hypotension (e.g., concomitant use of antihypertensives, dehydration and hypovolemia).

5.4 Seizures

Seizure has been estimated to occur in association with clozapine use at a cumulative incidence at 1 year of approximately 5%, based on the occurrence of 1 or more seizures in 61 of 1743 patients exposed to clozapine during its clinical testing prior to domestic marketing (i.e., a crude rate of 3.5%). The risk of seizure is dose-related. Initiate treatment with a low dose (12.5 mg), titrate slowly, and use divided dosing.

Use caution when administering CLOZARIL to patients with a history of seizures or other predisposing risk factors for seizure (e.g., head trauma or other CNS pathology, use of medications that lower the seizure threshold, or alcohol abuse). Because of the substantial risk of seizure associated with CLOZARIL use, caution patients about engaging in any activity where sudden loss of consciousness could cause serious risk to themselves or others (e.g., driving an automobile, operating complex machinery, swimming, climbing).

5.5 Myocarditis and Cardiomyopathy

Myocarditis and cardiomyopathy have occurred with the use of CLOZARIL. These reactions can be fatal. Discontinue CLOZARIL and obtain a cardiac evaluation upon suspicion of myocarditis or cardiomyopathy. Generally, patients with a history of clozapine-associated myocarditis or cardiomyopathy should not be rechallenged with CLOZARIL. However, if the benefit of CLOZARIL treatment is judged to outweigh the potential risks of recurrent myocarditis or cardiomyopathy, the clinician may consider rechallenge with CLOZARIL in consultation with a cardiologist, after a complete cardiac evaluation, and under close monitoring.

Consider the possibility of myocarditis or cardiomyopathy in patients receiving CLOZARIL who present with chest pain, dyspnea, persistent tachycardia at rest, palpitations, fever, flu-like symptoms, hypotension, other signs or symptoms of heart failure, or electrocardiographic findings (low voltages, ST-T abnormalities, arrhythmias, right axis deviation, and poor R wave progression). Myocarditis most frequently presents within the first 2 months of clozapine treatment. Symptoms of cardiomyopathy generally occur later than clozapine-associated myocarditis and usually after 8 weeks of treatment. However, myocarditis and cardiomyopathy can occur at any period during treatment with CLOZARIL. It is common for nonspecific flu-like symptoms such as malaise, myalgia, pleuritic chest pain, and low-grade fevers to precede more overt signs of heart failure. Typical laboratory findings include elevated troponin I or T, elevated creatinine kinase-MB, peripheral eosinophilia, and elevated C-reactive protein (CRP). Chest roentgenogram may demonstrate cardiac silhouette enlargement, and cardiac imaging (echocardiogram, radionucleotide studies, or cardiac catheterization) may reveal evidence of left ventricular dysfunction.

5.6 Increased Mortality in Elderly Patients with Dementia-Related Psychosis

Elderly patients with dementia-related psychosis treated with antipsychotic drugs are at an increased risk of death. Analyses of 17 placebo-controlled trials (modal duration of 10 weeks), largely in patients taking atypical antipsychotic drugs, revealed a risk of death in drug-treated patients of between 1.6 to 1.7 times the risk of death in placebo-treated patients. Over the course of a typical 10-week controlled trial, the rate of death in drug-treated patients was about 4.5%, compared to a rate of about 2.6% in the placebo group. Although the causes of death were varied, most of the deaths appeared to be either cardiovascular (e.g., heart failure, sudden death) or infectious (e.g., pneumonia) in nature. Observational studies suggest that, similar to atypical antipsychotic drugs, treatment with conventional antipsychotic drugs may increase mortality in this population. The extent to which the findings of increased mortality in observational studies may be attributed to the antipsychotic drug as opposed to some characteristic(s) of the patients is not clear. CLOZARIL is not approved for the treatment of patients with dementia-related psychosis . [see Boxed Warning]

5.7 Eosinophilia

Eosinophilia, defined as a blood eosinophil count of greater than 700/mm , has occurred with CLOZARIL treatment. In clinical trials, approximately 1% of patients developed eosinophilia. Clozapine-related eosinophilia usually occurs during the first month of treatment. In some patients, it has been associated with myocarditis, pancreatitis, hepatitis, colitis, and nephritis. Such organ involvement could be consistent with a drug reaction with eosinophilia and systemic symptoms (DRESS) syndrome, also known as drug induced hypersensitivity syndrome (DIHS). If eosinophilia develops during CLOZARIL treatment, evaluate promptly for signs and symptoms of systemic reactions, such as rash or other allergic symptoms, myocarditis, or other organ-specific disease associated with eosinophilia. If CLOZARIL-related systemic disease is suspected, discontinue CLOZARIL immediately.^3

If a cause of eosinophilia unrelated to CLOZARIL is identified (e.g., asthma, allergies, collagen vascular disease, parasitic infections, and specific neoplasms), treat the underlying cause and continue CLOZARIL.

Clozapine-related eosinophilia has also occurred in the absence of organ involvement and can resolve without intervention. There are reports of successful rechallenge after discontinuation of clozapine, without recurrence of eosinophilia. In the absence of organ involvement, continue CLOZARIL under careful monitoring. If the total eosinophil count continues to increase over several weeks in the absence of systemic disease, the decision to interrupt CLOZARIL therapy and rechallenge after the eosinophil count decreases should be based on the overall clinical assessment, in consultation with an internist or hematologist.

5.8 QT Interval Prolongation

QT prolongation, Torsades de Pointes and other life-threatening ventricular arrhythmias, cardiac arrest, and sudden death have occurred with CLOZARIL treatment. When prescribing CLOZARIL, consider the presence of additional risk factors for QT prolongation and serious cardiovascular reactions. Conditions that increase these risks include the following: history of QT prolongation, long QT syndrome, family history of long QT syndrome or sudden cardiac death, significant cardiac arrhythmia, recent myocardial infarction, uncompensated heart failure, treatment with other medications that cause QT prolongation, treatment with medications that inhibit the metabolism of clozapine, and electrolyte abnormalities.

Prior to initiating treatment with CLOZARIL, perform a careful physical examination, medical history, and concomitant medication history. Consider obtaining a baseline ECG and serum chemistry panel. Correct electrolyte abnormalities. Discontinue CLOZARIL if the QTc interval exceeds 500 msec. If patients experience symptoms consistent with Torsades de Pointes, or other arrhythmias, (e.g., syncope, presyncope, dizziness, or palpitations), obtain a cardiac evaluation and discontinue CLOZARIL.

Use caution when administering concomitant medications that prolong the QT interval or inhibit the metabolism of CLOZARIL. Drugs that cause QT prolongation include: specific antipsychotics (e.g., ziprasidone, iloperidone, chlorpromazine, thioridazine, mesoridazine, droperidol, pimozide), specific antibiotics (e.g., erythromycin, gatifloxacin, moxifloxacin, sparfloxacin), Class 1A antiarrhythmic medications (e.g., quinidine, procainamide) or Class III antiarrhythmics (e.g., amiodarone, sotalol), and others (e.g., pentamidine, levomethadyl acetate, methadone, halofantrine, mefloquine, dolasetron mesylate, probucol or tacrolimus). Clozapine is primarily metabolized by CYP isoenzymes 1A2, 2D6, and 3A4. Concomitant treatment with inhibitors of these enzymes can increase the concentration of CLOZARIL . [see Drug Interactions (7.1) and Clinical Pharmacology (12.3)]

Hypokalemia and hypomagnesemia increase the risk of QT prolongation. Hypokalemia can result from diuretic therapy, diarrhea, and other causes. Use caution when treating patients at risk for significant electrolyte disturbance, particularly hypokalemia. Obtain baseline measurements of serum potassium and magnesium levels, and periodically monitor electrolytes. Correct electrolyte abnormalities before initiating treatment with CLOZARIL.

5.9 Metabolic Changes

Atypical antipsychotic drugs, including CLOZARIL have been associated with metabolic changes that can increase cardiovascular and cerebrovascular risk. These metabolic changes include hyperglycemia, dyslipidemia, and body weight gain. While atypical antipsychotic drugs may produce some metabolic changes, each drug in the class has its own specific risk profile.

Hyperglycemia and Diabetes Mellitus

Hyperglycemia, in some cases extreme and associated with ketoacidosis or hyperosmolar coma or death, has been reported in patients treated with atypical antipsychotics including CLOZARIL. Assessment of the relationship between atypical antipsychotic use and glucose abnormalities is complicated by the possibility of an increased background risk of diabetes mellitus in patients with schizophrenia and the increasing incidence of diabetes mellitus in the general population. Given these confounders, the relationship between atypical antipsychotic use and hyperglycemia-related adverse reactions is not completely understood. However, epidemiological studies suggest an increased risk of treatment-emergent, hyperglycemia-related adverse reactions in patients treated with the atypical antipsychotics. Precise risk estimates for hyperglycemia-related adverse reactions in patients treated with atypical antipsychotics are not available.

Patients with an established diagnosis of diabetes mellitus who are started on CLOZARIL should be monitored regularly for worsening of glucose control. Patients with risk factors for diabetes mellitus (e.g., obesity, family history of diabetes) who are starting treatment with atypical antipsychotics should undergo fasting blood glucose testing at the beginning of treatment and periodically during treatment. Any patient treated with atypical antipsychotics should be monitored for symptoms of hyperglycemia including polydipsia, polyuria, polyphagia, and weakness. Patients who develop symptoms of hyperglycemia during treatment with atypical antipsychotics should undergo fasting blood glucose testing. In some cases, hyperglycemia has resolved when the atypical antipsychotic was discontinued; however, some patients required continuation of anti-diabetic treatment despite discontinuation of the suspect drug.

In a pooled data analysis of 8 studies in adult subjects with schizophrenia, the mean changes in fasting glucose concentration in the CLOZARIL and chlorpromazine groups were +11 mg/dL and +4 mg/dL respectively. A higher proportion of the CLOZARIL group demonstrated categorical increases from baseline in fasting glucose concentrations, compared to the chlorpromazine group (Table 3). The CLOZARIL doses were 100–900 mg per day (mean modal dose: 512 mg per day). The maximum chlorpromazine dose was 1800 mg per day (mean modal dose: 1029 mg per day). The median duration of exposure was 42 days for CLOZARIL and chlorpromazine.

Table 3. Categorical Changes in Fasting Glucose Level in Studies in Adult Subjects with Schizophrenia
Laboratory Parameter | Category Change (at least once) from baseline | Treatment Arm | N | n (%)
Fasting Glucose | Normal (<100 mg/dL) to High (≥126 mg/dL) | CLOZARIL | 198 | 53 (27)
Fasting Glucose | Normal (<100 mg/dL) to High (≥126 mg/dL) | Chlorpromazine | 135 | 14 (10)
Fasting Glucose | Borderline (100 to 125 mg/dL) to High (≥126 mg/dL) | CLOZARIL | 57 | 24 (42)
Fasting Glucose | Borderline (100 to 125 mg/dL) to High (≥126 mg/dL) | Chlorpromazine | 43 | 12 (28)

Dyslipidemia

Undesirable alterations in lipids have occurred in patients treated with atypical antipsychotics, including CLOZARIL. Clinical monitoring, including baseline and periodic follow-up lipid evaluations in patients using CLOZARIL, is recommended.

In a pooled data analysis of 10 studies in adult subjects with schizophrenia, CLOZARIL treatment was associated with increases in serum total cholesterol. No data were collected on LDL and HDL cholesterol. The mean increase in total cholesterol was 13 mg/dL in the CLOZARIL group and 15 mg/dL in the chlorpromazine group. In a pooled data analysis of 2 studies in adult subjects with schizophrenia, CLOZARIL treatment was associated with increases in fasting serum triglyceride. The mean increase in fasting triglyceride was 71 mg/dL (54%) in the CLOZARIL group and 39 mg/dL (35%) in the chlorpromazine group (Table 4). In addition, CLOZARIL treatment was associated with categorical increases in serum total cholesterol and triglyceride, as illustrated in Table 5.The proportion of patients with categorical increases in total cholesterol or fasting triglyceride increased with the duration of exposure. The median duration of CLOZARIL and chlorpromazine exposure was 45 days and 38 days, respectively. The CLOZARIL dose range was 100 mg to 900 mg daily; the maximum chlorpromazine dose was 1800 mg daily.

Table 4. Mean Changes in Total Cholesterol and Triglyceride Concentration in Studies in Adult Subjects with Schizophrenia
Treatment Arm | Baseline total cholesterol concentration (mg/dL) | Change from baseline mg/dL (%)
CLOZARIL (N=334) | 184 | +13 (7)
Chlorpromazine (185) | 182 | +15 (8)
 | Baseline triglyceride concentration (mg/dL) | Change from baseline mg/dL (%)
CLOZARIL (N=6) | 130 | +71 (54)
Chlorpromazine (N=7) | 110 | +39 (35)

Table 5. Categorical Changes in Lipid Concentrations in Studies in Adult Subjects with Schizophrenia
Laboratory Parameter | Category Change (at least once) from baseline | Treatment Arm | N | n (%)
Total Cholesterol (random or fasting) | Increase by ≥40 mg/dL | CLOZARIL | 334 | 111 (33)
Total Cholesterol (random or fasting) | Increase by ≥40 mg/dL | Chlorpromazine | 185 | 46 (25)
Total Cholesterol (random or fasting) | Normal (<200 mg/dL) to High (≥240 mg/dL) | CLOZARIL | 222 | 18 (8)
Total Cholesterol (random or fasting) | Normal (<200 mg/dL) to High (≥240 mg/dL) | Chlorpromazine | 132 | 3 (2)
Total Cholesterol (random or fasting) | Borderline (200-239 mg/dL) to High (≥240 mg/dL) | CLOZARIL | 79 | 30 (38)
Total Cholesterol (random or fasting) | Borderline (200-239 mg/dL) to High (≥240 mg/dL) | Chlorpromazine | 34 | 14 (41)
Triglycerides (fasting) | Increase by ≥50 mg/dL | CLOZARIL | 6 | 3 (50)
Triglycerides (fasting) | Increase by ≥50 mg/dL | Chlorpromazine | 7 | 3 (43)
Triglycerides (fasting) | Normal (<150 mg/dL) to High (≥200 mg/dL) | CLOZARIL | 4 | 0 (0)
Triglycerides (fasting) | Normal (<150 mg/dL) to High (≥200 mg/dL) | Chlorpromazine | 6 | 2 (33)
Triglycerides (fasting) | Borderline (≥150 mg/dL and <200 mg/dL) to High (≥200 mg/dL) | CLOZARIL | 1 | 1 (100)
Triglycerides (fasting) | Borderline (≥150 mg/dL and <200 mg/dL) to High (≥200 mg/dL) | Chlorpromazine | 1 | 0 (0)

Weight Gain

Weight gain has occurred with the use of antipsychotics, including CLOZARIL. Monitor weight during treatment with CLOZARIL. Table 6 summarizes the data on weight gain by the duration of exposure pooled from 11 studies with CLOZARIL and active comparators. The median duration of exposure was 609, 728, and 42 days, in the CLOZARIL, olanzapine, and chlorpromazine group, respectively.

Table 6. Mean Change in Body Weight (kg) by duration of exposure from studies in adult subjects with schizophrenia
Metabolic parameter | Exposure duration | CLOZARIL (N=669) |  | Olanzapine (N=442) |  | Chlorpromazine (N=155)
Metabolic parameter | Exposure duration | n | Mean | n | Mean | n | Mean
Weight change from baseline | 2 weeks (Day 11–17) | 6 | +0.9 | 3 | +0.7 | 2 | -0.5
Weight change from baseline | 4 weeks (Day 21–35) | 23 | +0.7 | 8 | +0.8 | 17 | +0.6
Weight change from baseline | 8 weeks (Day 49–63) | 12 | +1.9 | 13 | +1.8 | 16 | +0.9
Weight change from baseline | 12 weeks (Day 70–98) | 17 | +2.8 | 5 | +3.1 | 0 | 0
Weight change from baseline | 24 weeks (154–182) | 42 | - 0.6 | 12 | +5.7 | 0 | 0
Weight change from baseline | 48 weeks (Day 322–350) | 3 | +3.7 | 3 | +13.7 | 0 | 0

Table 7 summarizes pooled data from 11 studies in adult subjects with schizophrenia demonstrating weight gain ≥7% of body weight relative to baseline. The median duration of exposure was 609, 728, and 42 days, in the CLOZARIL, olanzapine, and chlorpromazine group, respectively.

Table 7. Proportion of Adult Subjects in Schizophrenia Studies with Weight Gain ≥7% Relative to Baseline Body Weight
Weight change | CLOZARIL | Olanzapine | Chlorpromazine
N | 669 | 442 | 155
≥7% (inclusive) | 236 (35%) | 203 (46%) | 13 (8%)

5.10 Neuroleptic Malignant Syndrome

Antipsychotic drugs including CLOZARIL can cause a potentially fatal symptom complex referred to as Neuroleptic Malignant Syndrome (NMS). Clinical manifestations of NMS include hyperpyrexia, muscle rigidity, altered mental status, and autonomic instability (irregular pulse or blood pressure, tachycardia, diaphoresis, and cardiac dysrhythmias). Associated findings can include elevated creatine phosphokinase (CPK), myoglobinuria, rhabdomyolysis, and acute renal failure.

The diagnostic evaluation of patients with this syndrome is complicated. It is important to consider the presence of other serious medical conditions (e.g., agranulocytosis, infection, heat stroke, primary CNS pathology, central anticholinergic toxicity, extrapyramidal symptoms, and drug fever).

The management of NMS should include (1) immediate discontinuation of antipsychotic drugs and other drugs not essential to concurrent therapy, (2) intensive symptomatic treatment and medical monitoring, and (3) treatment of comorbid medical conditions. There is no general agreement about specific pharmacological treatments for NMS.

If a patient requires antipsychotic drug treatment after recovery from NMS, the potential reintroduction of drug therapy should be carefully considered. NMS can recur. Monitor closely if restarting treatment with antipsychotics.

NMS has occurred with CLOZARIL monotherapy and with concomitant CNS-active medications, including lithium.

5.11 Fever

During clozapine therapy, patients have experienced transient, clozapine-related fever. The peak incidence is within the first 3 weeks of treatment. While this fever is generally benign and self-limited, it may necessitate discontinuing treatment. The fever can be associated with an increase or decrease in WBC count. Carefully evaluate patients with fever to rule out agranulocytosis or infection. Consider the possibility of NMS . [see Warnings and Precautions (5.10)]

5.12 Pulmonary Embolism

Pulmonary embolism and deep vein thrombosis have occurred in patients treated with CLOZARIL. Consider the possibility of pulmonary embolism in patients who present with deep-vein thrombosis, acute dyspnea, chest pain, or with other respiratory signs and symptoms. Whether pulmonary embolus and deep vein thrombosis can be attributed to clozapine or some characteristic(s) of patients is not clear.

5.13 Anticholinergic Toxicity

CLOZARIL has potent anticholinergic effects. Treatment with CLOZARIL can result in CNS and peripheral anticholinergic toxicity. Use with caution in the presence of narrow-angle glaucoma, concomitant anticholinergic medications, prostatic hypertrophy, or other conditions in which anticholinergic effects can lead to significant adverse reactions.

Treatment with CLOZARIL can result in gastrointestinal adverse reactions, including constipation, intestinal obstruction, fecal impaction, and paralytic ileus. Such reactions can be fatal. Constipation should be initially treated by ensuring adequate hydration and use of ancillary therapy such as bulk laxatives. Consultation with a gastroenterologist is advisable in more serious cases.

5.14 Interference with Cognitive and Motor Performance

CLOZARIL can cause sedation and impairment of cognitive and motor performance. Caution patients about operating hazardous machinery, including automobiles, until they are reasonably certain that CLOZARIL does not affect them adversely. These reactions may be dose-related. Consider reducing the dose if they occur.

5.15 Tardive Dyskinesia

Tardive dyskinesia (TD) has occurred in patients treated with antipsychotic drugs, including CLOZARIL. The syndrome consists of potentially irreversible, involuntary, dyskinetic movements. The risk of TD and the likelihood that it will become irreversible are believed to increase with greater durations of treatment and higher total cumulative doses. However, the syndrome can develop after relatively brief treatment periods at low doses. Prescribe CLOZARIL in a manner that is most likely to minimize the risk of developing TD. Use the lowest effective dose and the shortest duration necessary to control symptoms. Periodically assess the need for continued treatment. Consider discontinuing treatment if TD occurs. However, some patients may require treatment with CLOZARIL despite the presence of the syndrome.

There is no known treatment for TD. However, the syndrome may remit partially or completely if treatment is discontinued. Antipsychotic treatment, itself, may suppress (or partially suppress) the signs and symptoms, and it has the potential to mask the underlying process. The effect of symptom suppression on the long-term course of TD is unknown.

5.16 Cerebrovascular Adverse Reactions

In controlled trials, elderly patients with dementia-related psychosis treated with some atypical antipsychotics had an increased risk (compared to placebo) of cerebrovascular adverse reactions (e.g., stroke, transient ischemic attack), including fatalities. The mechanism for this increased risk is not known. An increased risk cannot be excluded for CLOZARIL or other antipsychotics or other patient populations. CLOZARIL should be used with caution in patients with risk factors for cerebrovascular adverse reactions.

5.17 Recurrence of Psychosis and Cholinergic Rebound after Abrupt Discontinuation of CLOZARIL

If abrupt discontinuation of CLOZARIL is necessary (because of agranulocytosis or another medical condition, for example), monitor carefully for the recurrence of psychotic symptoms and adverse reactions related to cholinergic rebound, such as profuse sweating, headache, nausea, vomiting and diarrhea.

6 ADVERSE REACTIONS

The following adverse reactions are discussed in more detail in other sections of the labeling:

- Agranulocytosis . [see Warnings and Precautions (5.1)]
- Orthostatic Hypotension, Bradycardia, and Syncope . [see Warnings and Precautions (5.3)]
- Seizures . [see Warnings and Precautions (5.4)]
- Myocarditis and Cardiomyopathy . [see Warnings and Precautions (5.5)]
- Increased Mortality in Elderly Patients with Dementia-Related Psychosis . [see Warnings and Precautions (5.6)]
- Eosinophilia . [see Warnings and Precautions (5.7)]
- QT Interval Prolongation . [see Warnings and Precautions (5.8)]
- Metabolic Changes (Hyperglycemia and Diabetes Mellitus, Dyslipidemia, and Weight Gain) . [see Warnings and Precautions (5.9)]
- Neuroleptic Malignant Syndrome . [see Warnings and Precautions (5.10)]
- Fever . [see Warnings and Precautions (5.11)]
- Pulmonary Embolism . [see Warnings and Precautions (5.12)]
- Anticholinergic Toxicity . [see Warnings and Precautions (5.13)]
- Interference with Cognitive and Motor Performance . [see Warnings and Precautions (5.14)]
- Tardive Dyskinesia . [see Warnings and Precautions (5.15)]
- Cerebrovascular Adverse Reactions . [see Warnings and Precautions (5.16)]
- Recurrence of Psychosis and Cholinergic Rebound after Abrupt Discontinuation . [see Warnings and Precautions (5.17)]

6.1 Clinical Trials Experience

Because clinical trials are conducted under widely varying conditions, adverse reaction rates observed in the clinical trials of a drug cannot be directly compared to rates in the clinical trials of another drug and may not reflect the rates observed in clinical practice.

The most commonly reported adverse reactions (>5%) across CLOZARIL clinical trials were: CNS reactions, including sedation, dizziness/vertigo, headache, and tremor; cardiovascular reactions, including tachycardia, hypotension, and syncope; autonomic nervous system reactions, including hypersalivation, sweating, dry mouth, and visual disturbances; gastrointestinal reactions, including constipation and nausea; and fever. Table 8 summarizes the most commonly reported adverse reactions (>5%) in CLOZARIL-treated patients (compared to chlorpromazine-treated patients) in the pivotal, 6-week, controlled trial in treatment-resistant schizophrenia.

Table 8. Common Adverse Reactions (≥5%) in the 6-Week, Randomized, Chlorpromazine-controlled Trial in Treatment-Resistant Schizophrenia
Adverse Reaction | CLOZARIL (N=126) (%) | Chlorpromazine (N=142) (%)
Sedation | 21 | 13
Tachycardia | 17 | 11
Constipation | 16 | 12
Dizziness | 14 | 16
Hypotension | 13 | 38
Fever (hyperthermia) | 13 | 4
Hypersalivation | 13 | 1
Hypertension | 12 | 5
Headache | 10 | 10
Nausea/vomiting | 10 | 12
Dry mouth | 5 | 20

Table 9 summarizes the adverse reactions reported in CLOZARIL-treated patients at a frequency of 2% or greater across all CLOZARIL studies (excluding the 2-year InterSePT™ Study). These rates are not adjusted for duration of exposure.

Table 9. Adverse Reactions (≥2%) Reported in CLOZARIL-treated Patients (N=842) Across all CLOZARIL Studies (excluding the 2-year InterSePT Study)TM
Body System Adverse Reaction* | CLOZARIL N=842 Percentage of Patients
Central Nervous System
Drowsiness/Sedation | 39
Dizziness/Vertigo | 19
Headache | 7
Tremor | 6
Syncope | 6
Disturbed Sleep/Nightmares | 4
Restlessness | 4
Hypokinesia/Akinesia | 4
Agitation | 4
Seizures (convulsions) | 3†
Rigidity | 3
Akathisia | 3
Confusion | 3
Fatigue | 2
Insomnia | 2
Cardiovascular
Tachycardia | 25†
Hypotension | 9
Hypertension | 4
Gastrointestinal
Constipation | 14
Nausea | 5
Abdominal Discomfort/Heartburn | 4
Nausea/Vomiting | 3
Vomiting | 3
Diarrhea | 2
Urogenital
Urinary Abnormalities | 2
Autonomic Nervous System
Salivation | 31
Sweating | 6
Dry Mouth | 6
Visual Disturbances | 5
Skin
Rash | 2
Hemic/Lymphatic
Leukopenia/Decreased WBC/Neutropenia | 3
Miscellaneous
Fever | 5
Weight Gain | 4
† Rate based on population of approximately 1700 exposed during premarket clinical evaluation of CLOZARIL.

Table 10 summarizes the most commonly reported adverse reactions (>10% of the CLOZARIL or olanzapine group) in the InterSePT Study. This was an adequate and well-controlled, 2-year study evaluating the efficacy of CLOZARIL relative to olanzapine in reducing the risk of suicidal behavior in patients with schizophrenia or schizoaffective disorder. The rates are not adjusted for duration of exposure.TM

Table 10. Incidence of Adverse Reactions in Patients Treated with CLOZARIL or Olanzapine in the InterSePT Study (>10% in the CLOZARIL or olanzapine group)TM
Adverse Reactions | CLOZARILN=479 % Reporting | Olanzapine N=477% Reporting
Salivary hypersecretion | 48 | 6
Somnolence | 46 | 25
Weight increased | 31 | 56
Dizziness (excluding vertigo) | 27 | 12
Constipation | 25 | 10
Insomnia | 20 | 33
Nausea | 17 | 10
Vomiting | 17 | 9
Dyspepsia | 14 | 8

Dystonia

Symptoms of dystonia, prolonged abnormal contractions of muscle groups, may occur in susceptible individuals during the first few days of treatment. Dystonic symptoms include: spasm of the neck muscles, sometimes progressing to tightness of the throat, swallowing difficulty, difficulty breathing, and/or protrusion of the tongue. While these symptoms can occur at low doses, they occur more frequently and with greater severity with high potency and at higher doses of first generation antipsychotic drugs. An elevated risk of acute dystonia is observed in males and younger age groups. Class effect:

6.2 Postmarketing Experience

The following adverse reactions have been identified during post-approval use of clozapine. Because these reactions are reported voluntarily from a population of uncertain size, it is not always possible to reliably estimate their frequency or establish a causal relationship to drug exposure.

Central Nervous System

Delirium, EEG abnormal, myoclonus, paresthesia, possible cataplexy, status epilepticus, obsessive compulsive symptoms, and post-discontinuation cholinergic rebound adverse reactions.

Cardiovascular System

Atrial or ventricular fibrillation, ventricular tachycardia, QT interval prolongation, Torsades de Pointes, myocardial infarction, cardiac arrest, and periorbital edema.

Gastrointestinal System

Acute pancreatitis, dysphagia, salivary gland swelling.

Hepatobiliary System

Cholestasis, hepatitis, jaundice, hepatotoxicity, hepatic steatosis, hepatic necrosis, hepatic fibrosis, hepatic cirrhosis, liver injury (hepatic, cholestatic, and mixed), and liver failure.

Urogenital System

Acute interstitial nephritis, nocturnal enuresis, priapism, and renal failure.

Skin

Hypersensitivity reactions: photosensitivity, vasculitis, erythema multiforme, and Stevens-Johnson Syndrome.

Musculoskeletal System

Myasthenic syndrome and rhabdomyolysis.

Respiratory System

Aspiration, pleural effusion, pneumonia, lower respiratory tract infection.

Hemic and Lymphatic System

Deep-vein thrombosis, elevated hemoglobin/hematocrit, erythrocyte sedimentation rate (ESR) increased, sepsis, thrombocytosis, and thrombocytopenia.

Vision Disorders

Narrow-angle glaucoma.

Miscellaneous

Creatine phosphokinase elevation, hyperuricemia, hyponatremia, and weight loss.

7 DRUG INTERACTIONS

7.1 Potential for Other Drugs to Affect CLOZARIL

Clozapine is a substrate for many cytochrome P450 isozymes, in particular CYP1A2, CYP3A4, and CYP2D6. Use caution when administering CLOZARIL concomitantly with drugs that are inducers or inhibitors of these enzymes.

CYP1A2 Inhibitors

Concomitant use of CLOZARIL and CYP1A2 inhibitors can increase plasma levels of clozapine, potentially resulting in adverse reactions. Reduce the CLOZARIL dose to one-third of the original dose when CLOZARIL is coadministered with strong CYP1A2 inhibitors (e.g., fluvoxamine, ciprofloxacin, or enoxacin). The CLOZARIL dose should be increased to the original dose when coadministration of strong CYP1A2 inhibitors is discontinued . [see Dosage and Administration (2.6), Clinical Pharmacology (12.3)]

Moderate or weak CYP1A2 inhibitors include oral contraceptives and caffeine. Monitor patients closely when CLOZARIL is coadministered with these inhibitors. Consider reducing the CLOZARIL dosage if necessary . [see Dosage and Administration (2.6)]

CYP2D6 and CYP3A4 Inhibitors

Concomitant treatment with CLOZARIL and CYP2D6 or CYP3A4 inhibitors (e.g., cimetidine, escitalopram, erythromycin, paroxetine, bupropion, fluoxetine, quinidine, duloxetine, terbinafine, or sertraline) can increase clozapine levels and lead to adverse reactions . Use caution and monitor patients closely when using such inhibitors. Consider reducing the CLOZARIL dose . [see Clinical Pharmacology (12.3)] [see Dosage and Administration (2.6)]

CYP1A2 and CYP3A4 Inducers

Concomitant treatment with drugs that induce CYP1A2 or CYP3A4 can decrease the plasma concentration of clozapine, resulting in decreased effectiveness of CLOZARIL. Tobacco smoke is a moderate inducer of CYP1A2. Strong CYP3A4 inducers include carbamazepine, phenytoin, St. John’s wort, and rifampin. It may be necessary to increase the CLOZARIL dose if used concomitantly with inducers of these enzymes. However, concomitant use of CLOZARIL and strong CYP3A4 inducers is not recommended . [see Dosage and Administration (2.6)]

Consider reducing the CLOZARIL dosage when discontinuing coadministered enzyme inducers; because discontinuation of inducers can result in increased clozapine plasma levels and an increased risk of adverse reactions . [see Dosage and Administration (2.6)]

Drugs that Cause QT Interval Prolongation

Use caution when administering concomitant medications that prolong the QT interval or inhibit the metabolism of clozapine. Drugs that cause QT prolongation include: specific antipsychotics (e.g., ziprasidone, iloperidone, chlorpromazine, thioridazine, mesoridazine, droperidol, and pimozide), specific antibiotics (e.g., erythromycin, gatifloxacin, moxifloxacin, sparfloxacin), Class 1A antiarrhythmics (e.g., quinidine, procainamide) or Class III antiarrhythmics (e.g., amiodarone, sotalol), and others (e.g., pentamidine, levomethadyl acetate, methadone, halofantrine, mefloquine, dolasetron mesylate, probucol or tacrolimus) . [see Warnings and Precautions (5.8)]

7.2 Potential for CLOZARIL to Affect Other Drugs

Concomitant use of CLOZARIL with other drugs metabolized by CYP2D6 can increase levels of these CYPD26 substrates. Use caution when coadministering CLOZARIL with other drugs that are metabolized by CYP2D6. It may be necessary to use lower doses of such drugs than usually prescribed. Such drugs include specific antidepressants, phenothiazines, carbamazepine, and Type 1C antiarrhythmics (e.g., propafenone, flecainide, and encainide).

8 USE IN SPECIFIC POPULATIONS

8.1 Pregnancy

Pregnancy Category B

Risk Summary

There are no adequate or well-controlled studies of clozapine in pregnant women.

Reproduction studies have been performed in rats and rabbits at doses up to 0.4 and 0.9 times, respectively, the maximum recommended human dose (MRHD) of 900 mg/day on a mg/m body surface area basis. The studies revealed no evidence of impaired fertility or harm to the fetus due to clozapine. Because animal reproduction studies are not always predictive of human response, CLOZARIL should be used during pregnancy only if clearly needed.^2

Clinical Considerations

Consider the risk of exacerbation of psychosis when discontinuing or changing treatment with antipsychotic medications during pregnancy and postpartum. Consider early screening for gestational diabetes for patients treated with antipsychotic medications . Neonates exposed to antipsychotic drugs during the third trimester of pregnancy are at risk for extrapyramidal and/or withdrawal symptoms following delivery. Monitor neonates for symptoms of agitation, hypertonia, hypotonia, tremor, somnolence, respiratory distress, and feeding difficulties. The severity of complications can vary from self-limited symptoms to some neonates requiring intensive care unit support and prolonged hospitalization. [see Warnings and Precautions (5.9)]

Animal Data

In embryofetal developmental studies, clozapine had no effects on maternal parameters, litter sizes, or fetal parameters when administered orally to pregnant rats and rabbits during the period of organogenesis at doses up to 0.4 and 0.9 times, respectively, the MRHD of 900 mg/day on a mg/m body surface area basis.^2

In peri/postnatal developmental studies, pregnant female rats were administered clozapine over the last third of pregnancy and until day 21 postpartum. Observations were made on fetuses at birth and during the postnatal period; the offspring were allowed to reach sexual maturity and mated. Clozapine caused a decrease in maternal body weight but had no effects on litter size or body weights of either F1or F2 generations at doses up to 0.4 times the MRHD of 900 mg/day on a mg/m body surface area basis.^2

8.3 Nursing Mothers

CLOZARIL is present in human milk. Because of the potential for serious adverse reactions in nursing infants from CLOZARIL, a decision should be made whether to discontinue nursing or to discontinue the drug, taking into account the importance of the drug to the mother.

8.4 Pediatric Use

Safety and effectiveness in pediatric patients have not been established.

8.5 Geriatric Use

There have not been sufficient numbers of geriatric patients in clinical studies utilizing CLOZARIL to determine whether those over 65 years of age differ from younger subjects in their response to CLOZARIL.

Orthostatic hypotension and tachycardia can occur with CLOZARIL treatment . Elderly patients, particularly those with compromised cardiovascular functioning, may be more susceptible to these effects. [see Boxed Warning and Warnings and Precautions (5.3)]

Elderly patients may be particularly susceptible to the anticholinergic effects of CLOZARIL, such as urinary retention and constipation . [see Warnings and Precautions (5.13)]

Carefully select CLOZARIL doses in elderly patients, taking into consideration their greater frequency of decreased hepatic, renal, or cardiac function, as well as other concomitant disease and other drug therapy. Clinical experience suggests that the prevalence of tardive dyskinesia appears to be highest among the elderly; especially elderly women . [see Warnings and Precautions (5.15)]

8.6 Patients with Renal or Hepatic Impairment

Dose reduction may be necessary in patients with significant impairment of renal or hepatic function. Clozapine concentrations may be increased in these patients, because clozapine is almost completely metabolized and then excreted . [see Dosage and Administration (2.7), Clinical Pharmacology (12.3)]

8.7 CYP2D6 Poor Metabolizers

Dose reduction may be necessary in patients who are CYP2D6 poor metabolizers. Clozapine concentrations may be increased in these patients, because clozapine is almost completely metabolized and then excreted . [see Dosage and Administration (2.7), Clinical Pharmacology (12.3)]

10 OVERDOSAGE

10.1 Overdosage Experience

The most commonly reported signs and symptoms associated with clozapine overdose are: sedation, delirium, coma, tachycardia, hypotension, respiratory depression or failure; and hypersalivation. There are reports of aspiration pneumonia, cardiac arrhythmias, and seizure. Fatal overdoses have been reported with clozapine, generally at doses above 2500 mg. There have also been reports of patients recovering from overdoses well in excess of 4 g.

10.2 Management of Overdosage

For the most up-to-date information on the management of CLOZARIL overdosage, contact a certified Regional Poison Control Center (1-800-222-1222). Telephone numbers of certified Regional Poison Control Centers are listed in the , a registered trademark of Thomson PDR. Establish and maintain an airway; ensure adequate oxygenation and ventilation. Monitor cardiac status and vital signs. Use general symptomatic and supportive measures. There are no specific antidotes for CLOZARIL. **Physicians’ Desk Reference®

In managing overdosage, consider the possibility of multiple-drug involvement.

11 DESCRIPTION

CLOZARIL (clozapine), an atypical antipsychotic drug, is a tricyclic dibenzodiazepine derivative, 8-chloro-11-(4-methyl-1-piperazinyl)-5H-dibenzo [b,e] [1,4] diazepine. The structural formula is:®

CLOZARIL is available in pale yellow tablets of 25 mg and 100 mg for oral administration.

Active Ingredient: clozapine

Inactive Ingredients: colloidal silicon dioxide, lactose, magnesium stearate, povidone, starch (corn), and talc.

12 CLINICAL PHARMACOLOGY

12.1 Mechanism of Action

The mechanism of action of clozapine is unknown. However, it has been proposed that the therapeutic efficacy of clozapine in schizophrenia is mediated through antagonism of the dopamine type 2 (D) and the serotonin type 2A (5-HT) receptors. CLOZARIL also acts as an antagonist at adrenergic, cholinergic, histaminergic and other dopaminergic and serotonergic receptors.22A

12.2 Pharmacodynamics

Clozapine demonstrated binding affinity to the following receptors: histamine H (K 1.1 nM), adrenergic α (K 1.6 nM), serotonin 5-HT (K 4 nM), serotonin 5-HT (K 5.4 nM), muscarinic M (K 6.2 nM), serotonin 5-HT (K 6.3 nM), serotonin 5-HT (K 9.4 nM), dopamine D (K 24 nM), adrenergic α (K 90 nM), serotonin 5-HT (K 95 nM), serotonin 5-HT (K 120 nM), dopamine D (K 160 nM), dopamine D (K 270 nM), dopamine D (K 454 nM), and dopamine D (K 555 nM).1i1Ai6i2Ai1i7i2Ci4i2Ai3i1Ai2i1i5i3i

Clozapine causes little or no prolactin elevation.

Clinical electroencephalogram (EEG) studies demonstrated that clozapine increases delta and theta activity and slows dominant alpha frequencies. Enhanced synchronization occurs. Sharp wave activity and spike and wave complexes may also develop. Patients have reported an intensification of dream activity during clozapine therapy. REM sleep was found to be increased to 85% of the total sleep time. In these patients, the onset of REM sleep occurred almost immediately after falling asleep.

12.3 Pharmacokinetics

Absorption

In man, CLOZARIL tablets (25 mg and 100 mg) are equally bioavailable relative to a CLOZARIL solution. Following oral administration of CLOZARIL 100 mg twice daily, the average steady-state peak plasma concentration was 319 ng/mL (range: 102 to 771 ng/mL), occurring at the average of 2.5 hours (range: 1 to 6 hours) after dosing. The average minimum concentration at steady state was 122 ng/mL (range: 41 to 343 ng/mL), after 100 mg twice daily dosing. Food does not appear to affect the systemic bioavailability of CLOZARIL. Thus, CLOZARIL may be administered with or without food.

Distribution

Clozapine is approximately 97% bound to serum proteins. The interaction between clozapine and other highly protein-bound drugs has not been fully evaluated but may be important . [see Drug Interactions (7)]

Metabolism and Excretion

Clozapine is almost completely metabolized prior to excretion, and only trace amounts of unchanged drug are detected in the urine and feces. Clozapine is a substrate for many cytochrome P450 isozymes, in particular CYP1A2, CYP2D6, and CYP3A4. Approximately 50% of the administered dose is excreted in the urine and 30% in the feces. The demethylated, hydroxylated, and N-oxide derivatives are components in both urine and feces. Pharmacological testing has shown the desmethyl metabolite (norclozapine) to have only limited activity, while the hydroxylated and oxide derivatives were inactive. The mean elimination half-life of clozapine after a single 75 mg dose was 8 hours (range: 4 to12 hours), compared to a mean elimination half-life of 12 hours (range: 4 to 66 hours), after achieving steady state with 100mg twice daily dosing. N-

A comparison of single-dose and multiple-dose administration of clozapine demonstrated that the elimination half-life increased significantly after multiple dosing relative to that after single-dose administration, suggesting the possibility of concentration-dependent pharmacokinetics. However, at steady state, approximately dose-proportional changes with respect to area under the curve (AUC), peak, and minimum clozapine plasma concentrations were observed after administration of 37.5, 75, and 150 mg twice daily.

Drug-Drug Interaction Studies

Fluvoxamine

A pharmacokinetic study was conducted in 16 schizophrenic patients who received clozapine under steady-state conditions. After coadministration of fluvoxamine for 14 days, mean trough concentrations of clozapine and its metabolites, N-desmethylclozapine and clozapine N-oxide, were elevated about 3-fold compared to baseline steady-state concentrations.

Paroxetine, Fluoxetine, and Sertraline

In a study of schizophrenic patients (n=14) who received clozapine under steady-state conditions, coadministration of paroxetine produced only minor changes in the levels of clozapine and its metabolites. However, other published reports describe modest elevations (less than 2-fold) of clozapine and metabolite concentrations when clozapine was taken with paroxetine, fluoxetine, and sertraline.

Specific Population Studies

Renal or Hepatic Impairment

No specific pharmacokinetic studies were conducted to investigate the effects of renal or hepatic impairment on the pharmacokinetics of clozapine. Higher clozapine plasma concentrations are likely in patients with significant renal or hepatic impairment when given usual doses.

CYP2D6 Poor Metabolizers

A subset (3%–10%) of the population has reduced activity of CYP2D6 (CYP2D6 poor metabolizers). These individuals may develop higher than expected plasma concentrations of clozapine when given usual doses.

13 NONCLINICAL TOXICOLOGY

13.1 Carcinogenesis, Mutagenesis, Impairment of Fertility

Carcinogenesis

No carcinogenic potential was demonstrated in long-term studies in mice and rats at doses up to 0.3 times and 0.4 times, respectively, the maximum recommended human dose (MRHD) of 900 mg/day on a mg/m body surface area basis.^2

Mutagenesis

Clozapine was not genotoxic when tested in the following gene mutation and chromosomal aberration tests: the bacterial Ames test, the mammalian V79 in Chinese hamster cells, the unscheduled DNA synthesis in rat hepatocytes or the micronucleus assay in mice. in vitroin vitroin vivo

Impairment of Fertility

Clozapine had no effect on any parameters of fertility, pregnancy, fetal weight or postnatal development when administered orally to male rats 70 days before mating and to female rats for 14 days before mating at doses up to 0.4 times the MRHD of 900 mg/day on a mg/m body surface area basis.^2

14 CLINICAL STUDIES

14.1 Treatment Resistant Schizophrenia

The efficacy of CLOZARIL in treatment-resistant schizophrenia was established in a multicenter, randomized, double-blind, active-controlled (chlorpromazine) study in patients with a DSM-III diagnosis of schizophrenia who had inadequate responses to at least 3 different antipsychotics (from at least 2 different chemical classes) during the preceding 5 years. The antipsychotic trials must have been judged adequate; the antipsychotic dosages must have been equivalent to or greater than 1000 mg per day of chlorpromazine for a period of at least 6 weeks, each without significant reduction of symptoms. There must have been no period of good functioning within the preceding 5 years. Patients must have had a baseline score of at least 45 on the investigator-rated Brief Psychiatric Rating Scale (BPRS). On the 18-item BPRS, 1 indicates the absence of symptoms, and 7 indicates severe symptoms; the maximum potential total BPRS score is 126. At baseline, the mean BPRS score was 61. In addition, patients must have had a score of at least 4 on at least 2 of the following 4 individual BPRS items: conceptual disorganization, suspiciousness, hallucinatory behavior, and unusual thought content. Patients must have had a Clinical Global Impressions–Severity Scale score of at least 4 (moderately ill).

In the prospective, lead-in phase of the trial, all patients (N=305) initially received single-blind treatment with haloperidol (the mean dose was 61 mg per day) for 6 weeks. More than 80% of patients completed the 6-week trial. Patients with an inadequate response to haloperidol (n=268) were randomized to double-blind treatment with CLOZARIL (N=126) or chlorpromazine (N=142). The maximum daily CLOZARIL dose was 900 mg; the mean daily dose was >600 mg. The maximum daily chlorpromazine dose was 1800 mg; the mean daily dose was >1200 mg.

The primary endpoint was treatment response, predefined as a decrease in BPRS score of at least 20% and either (1) a CGI-S score of <3 (mildly ill), or (2) a BPRS score of <35, at the end of 6 weeks of treatment. Approximately 88% of patients from the CLOZARIL and chlorpromazine groups completed the 6-week trial. At the end of 6 weeks, 30% of the CLOZARIL group responded to treatment, and 4% of the chlorpromazine group responded to treatment. The difference was statistically significant (p <0.001). The mean change in total BPRS score was -16 and -5 in the CLOZARIL and chlorpromazine group, respectively; the mean change in the 4 key BPRS item scores was -5 and -2 in the CLOZARIL and chlorpromazine group, respectively; and the mean change in CGI-S score was -1.2 and -0.4, in the CLOZARIL and chlorpromazine group, respectively. These changes in the CLOZARIL group were statistically significantly greater than in the chlorpromazine group (p<0.001 in each analysis).

14.2 Recurrent Suicidal Behavior in Schizophrenia or Schizoaffective Disorder

The effectiveness of CLOZARIL in reducing the risk of recurrent suicidal behavior was assessed in the International Suicide Prevention Trial (InterSePT™, a trademark of Novartis Pharmaceuticals Corporation). This was a prospective, randomized, open-label, active-controlled, multicenter, international, parallel-group comparison of CLOZARIL versus olanzapine (*Zyprexa®, a registered trademark of Eli Lilly and Company) in 956 patients with schizophrenia or schizoaffective disorder (DSM-IV) who were judged to be at risk for recurrent suicidal behavior. Only about one-fourth of these patients (27%) were considered resistant to standard antipsychotic drug treatment. To enter the trial, patients must have met 1 of the following criteria:

- They had attempted suicide within the 3 years prior to their baseline evaluation.
- They had been hospitalized to prevent a suicide attempt within the 3 years prior to their baseline evaluation.
- They demonstrated moderate-to-severe suicidal ideation with a depressive component within 1 week prior to their baseline evaluation.
- They demonstrated moderate-to-severe suicidal ideation accompanied by command hallucinations to do self-harm within 1 week prior to their baseline evaluation.

Dosing regimens for each treatment group were determined by individual investigators and were individualized by patient. Dosing was flexible, with a dose range of 200–900 mg/day for CLOZARIL and 5–20 mg/day for olanzapine. For the 956 patients who received CLOZARIL or olanzapine in this study, there was extensive use of concomitant psychotropics: 84% with antipsychotics, 65% with anxiolytics, 53% with antidepressants, and 28% with mood stabilizers. There was significantly greater use of concomitant psychotropic medications among the patients in the olanzapine group.

The primary efficacy measure was time to (1) a significant suicide attempt, including a completed suicide; (2) hospitalization due to imminent suicide risk, including increased level of surveillance for suicidality for patients already hospitalized; or (3) worsening of suicidality severity as demonstrated by “much worsening” or “very much worsening” from baseline in the Clinical Global Impression of Severity of Suicidality as assessed by the Blinded Psychiatrist (CGI-SS-BP) scale. A determination of whether or not a reported event met criterion 1 or 2 above was made by the Suicide Monitoring Board (SMB), a group of experts blinded to patient data.

A total of 980 patients were randomized to the study and 956 received study medication. Sixty-two percent of the patients were diagnosed with schizophrenia, and the remainder (38%) were diagnosed with schizoaffective disorder. Only about one-fourth of the total patient population (27%) was identified as “treatment-resistant” at baseline. There were more males than females in the study (61% of all patients were male). The mean age of patients entering the study was 37 years of age (range 18–69). Most patients were Caucasian (71%), 15% were black, 1% were Asian, and 13% were classified as being of “other” races.

Patients treated with CLOZARIL had a statistically significant longer delay in the time to recurrent suicidal behavior in comparison with olanzapine. This result should be interpreted only as evidence of the effectiveness of CLOZARIL in delaying time to recurrent suicidal behavior and not a demonstration of the superior efficacy of CLOZARIL over olanzapine.

The probability of experiencing (1) a significant suicide attempt, including a completed suicide, or (2) hospitalization because of imminent suicide risk, including increased level of surveillance for suicidality for patients already hospitalized, was lower for CLOZARIL patients than for olanzapine patients at Week 104: CLOZARIL 24% versus olanzapine 32%; 95% CI of the difference: 2%, 14% (Figure 2).

Figure 2. Cumulative Probability of a Significant Suicide Attempt or Hospitalization to Prevent Suicide in Patients with Schizophrenia or Schizoaffective Disorder at High Risk of Suicidality

16 HOW SUPPLIED/STORAGE AND HANDLING

NDC:64725-1260-1 in a CONTAINER of 30 TABLETS

16.1 How Supplied

CLOZARIL® (clozapine) is available as 25 mg and 100 mg round, pale-yellow, uncoated tablets with a facilitated score on one side.

CLOZARIL® (clozapine) Tablets

25 mg

Engraved with “CLOZARIL” once on the periphery of one side.

Engraved with a facilitated score and “25” once on the other side.

Bottle of 100

NDC 0078-0126-05

Bottle of 500

NDC 0078-0126-08

Unit dose packages of 100: 2 x 5 strips, 10 blisters per strip

NDC 0078-0126-06

100 mg

Engraved with “CLOZARIL” once on the periphery of one side.

Engraved with a facilitated score and “100” once on the other side.

Bottle of 100

NDC 0078-0127-05

Bottle of 500

NDC 0078-0127-08

Unit dose packages of 100: 2 x 5 strips, 10 blisters per strip

NDC 0078-0127-06

16.2 Storage and Handling

Storage temperature should not exceed 30°C (86°F).

Keep out of reach of children.

17 PATIENT COUNSELING INFORMATION

Discuss the following issues with patients and caregivers:

- Prior to initiating treatment, educate patients and caregivers about the significant risk of developing agranulocytosis. Advise them to immediately report the appearance of signs or symptoms consistent with agranulocytosis or infection (e.g., fever; mucus membrane ulcers; skin, pharyngeal, vaginal, urinary, or pulmonary infection; or extreme weakness or lethargy) at any time during CLOZARIL therapy . Agranulocytosis:[see Boxed Warning and Warnings and Precautions (5.1)]
  - Inform patients and caregivers that CLOZARIL will be made available only through a special program (CLOZARIL National Registry) designed to ensure the required blood monitoring, in order to reduce the risk of developing agranulocytosis. Inform patients and caregivers the WBC count and ANC will be monitored as follows:
    - Weekly blood tests are required for the first 6 months.
    - If acceptable WBC counts and ANCs (WBC count ≥3500/mm and ANC ≥2000/mm) have been maintained during the first 6 months of continuous therapy, then WBC counts and ANCs can be monitored every 2 weeks for the next 6 months.^3^3
    - Thereafter, if acceptable WBC counts and ANCs have been maintained during the second 6 months of continuous therapy, WBC counts and ANCs can be monitored every 4 weeks.
- Inform patients and caregivers about the risk of orthostatic hypotension and syncope, especially during the period of initial dose titration. Instruct them to strictly follow the clinician’s instructions for dosage and administration. Advise patients to consult their clinician immediately if they feel faint, lose consciousness or have signs or symptoms suggestive of bradycardia or arrhythmia . Orthostatic Hypotension, Bradycardia, and Syncope:[see Dosage and Administration (2.2) and Warnings and Precautions (5.3)]
- Inform patients and caregivers about the significant risk of seizure during CLOZARIL treatment. Caution them about driving and any other potentially hazardous activity while taking CLOZARIL . Seizures:[see Warnings and Precautions (5.4)]
- Advise patients to consult their clinician immediately if they feel faint, lose consciousness or have signs or symptoms suggestive of arrhythmia. Instruct patients to not take CLOZARIL with other drugs that cause QT interval prolongation. Instruct patients to inform their clinicians that they are taking CLOZARIL before any new drug . QT Interval Prolongation:[see Warnings and Precautions (5.8.) and Drug Interactions (7.1)]
- Educate patients and caregivers about the risk of metabolic changes and the need for specific monitoring. The risks include hyperglycemia and diabetes mellitus, dyslipidemia, weight gain, and cardiovascular reactions. Educate patients and caregivers about the symptoms of hyperglycemia (high blood sugar) and diabetes mellitus (e.g., polydipsia, polyuria, polyphagia, and weakness). Monitor all patients for these symptoms. Patients who are diagnosed with diabetes or have risk factors for diabetes (obesity, family history of diabetes) should have their fasting blood glucose monitored before beginning treatment and periodically during treatment. Patients who develop symptoms of hyperglycemia should have assessments of fasting glucose. Clinical monitoring of weight is recommended . Metabolic Changes (hyperglycemia and diabetes mellitus, dyslipidemia, weight gain):[see Warnings and Precautions (5.9)]
- Because CLOZARIL may have the potential to impair judgment, thinking, or motor skills, patients should be cautioned about operating hazardous machinery, including automobiles, until they are reasonably certain that CLOZARIL therapy does not affect them adversely . Interference with Cognitive and Motor Performance:[see Warnings and Precautions (5.14)]
- Inform patients and caregivers that if the patient misses taking CLOZARIL for more than 2 days, they should not restart their medication at the same dosage but should contact their physician for dosing instructions adversely . Missed Doses and Re-initiating Treatment:[see Dosage and Administration (2.5) and Warnings and Precautions (5.3)]
- Patients and caregivers should notify the clinician if the patient becomes pregnant or intends to become pregnant during therapy . Pregnancy:[see Use in Specific Populations (8.1)]
- Advice patients and caregivers that the patient should not breast feed an infant if they are taking CLOZARIL [see Use in Specific Populations (8.3)]. Nursing:
- Advise patients to inform their health care provider if they are taking, or plan to take, any prescription or over-the-counter drugs; there is a potential for significant drug-drug interactions . Concomitant Medication:[see Dosage and Administrations (2.6) and Drug Interactions (7.1)]

*Zyprexa® (olanzapine) is a registered trademark of Eli Lilly and Company.

**Trademark of Thomson Healthcare, Inc.

CLOZARIL® is a registered trademark of Novartis Pharmaceuticals Corporation.

Novartis Pharmaceuticals Corporation East Hanover, New Jersey 07936

© Novartis

T2013-114 November 2013